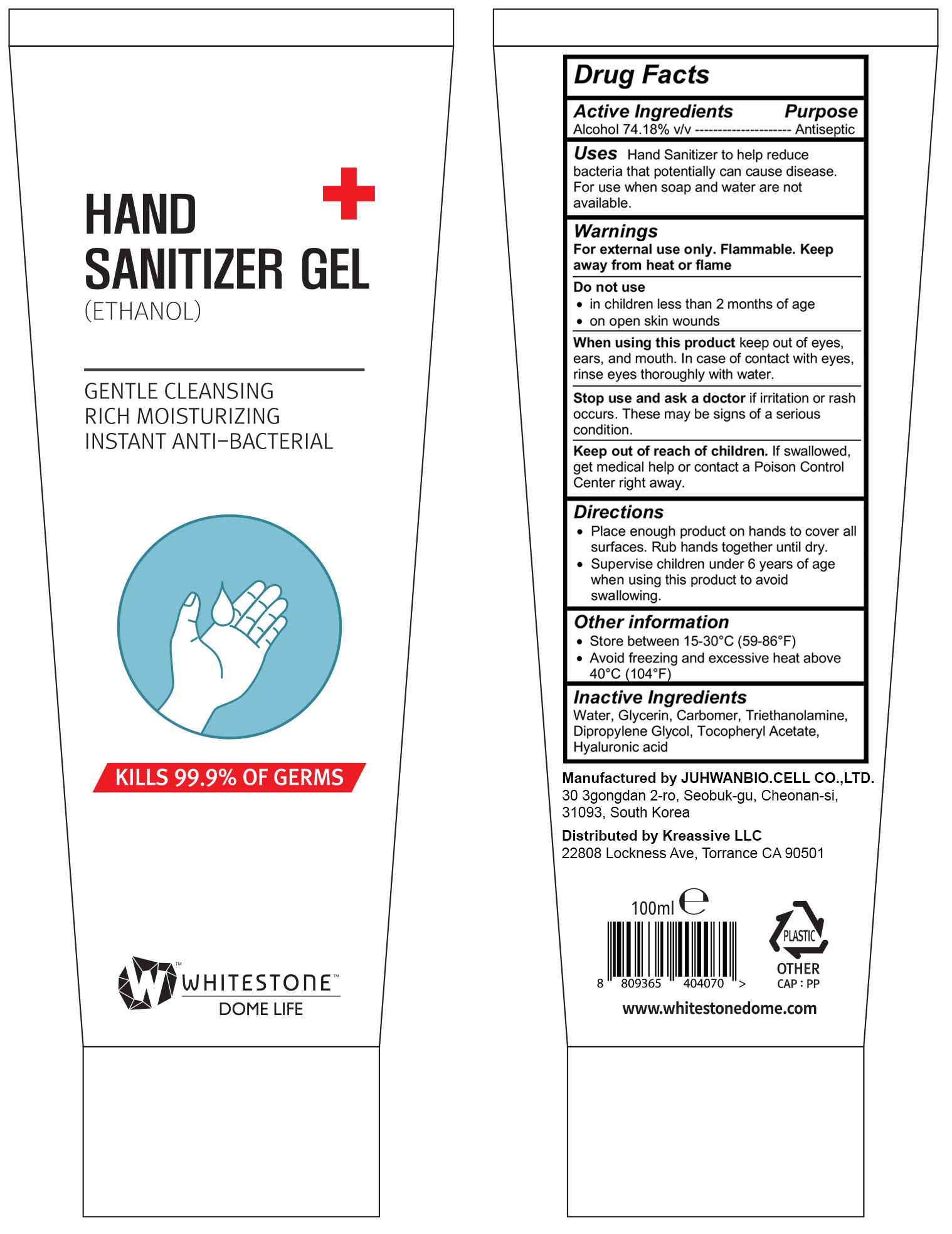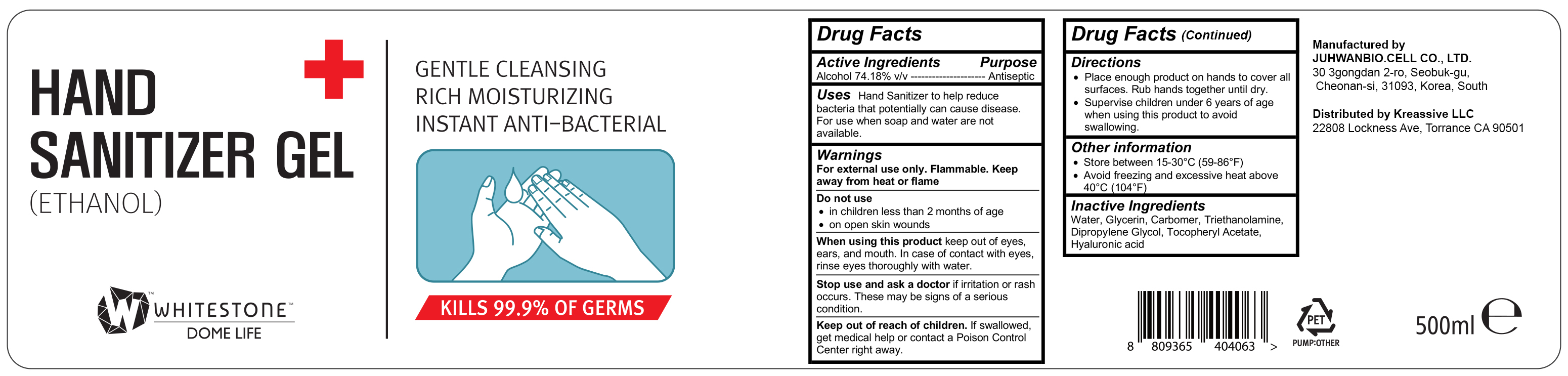 DRUG LABEL: Whitestone Dome Life Hand Sanitizer
NDC: 76941-101 | Form: GEL
Manufacturer: White Stone, Ltd.
Category: otc | Type: HUMAN OTC DRUG LABEL
Date: 20200428

ACTIVE INGREDIENTS: ALCOHOL 74.18 mL/100 mL
INACTIVE INGREDIENTS: .ALPHA.-TOCOPHEROL ACETATE; CARBOMER HOMOPOLYMER, UNSPECIFIED TYPE; WATER; TROLAMINE; DIPROPYLENE GLYCOL; HYALURONIC ACID; GLYCERIN

Whitestone Dome Life Hand Sanitizer

Active ingredient

Alcohol 74.18% v/v

Purpose

Antiseptic

Uses

Hand Sanitizer to help reduce bacteria that potentially can cause disease. For use when soap and water are not available.

Warnings

For external use only. Flammable. Keep away from heat or flame

Do not use

· in children less than 2 months of age

· on open skin wounds

When using this product keep out of eyes, ears, and mouth. In case of contact with eyes, rinse eyes thoroughly with water.

Stop use and ask a doctor if irritation or rash occurs. These may be signs of a serious condition.

Keep out of reach of children

If swallowed, get medical help or contact a Poison Control Center right away.

Directions

- Place enough product on hands to cover all surfaces. Rub hands together until dry.
- Supervise children under 6 years of age when using this product to avoid swallowing.

Inactive ingredients

Water, Glycerin, Carbomer, Triethanolamine, Dipropylene Glycol, Tocopheryl Acetate, Hyaluronic acid